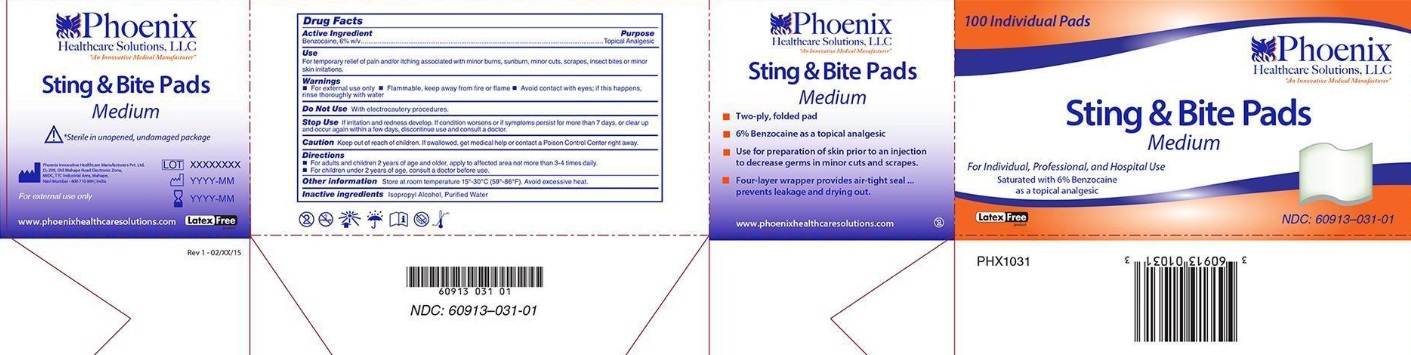 DRUG LABEL: Sting and Bite
NDC: 60913-031 | Form: SWAB
Manufacturer: PHOENIX HEALTHCARE SOLUTIONS, LLC
Category: otc | Type: HUMAN OTC DRUG LABEL
Date: 20251023

ACTIVE INGREDIENTS: BENZOCAINE 6 g/100 mL
INACTIVE INGREDIENTS: WATER; ISOPROPYL ALCOHOL

Phoenix Sting and Bite

Active Ingredient

Benzocaine, 6% w/v

Purpose

Topical Analgesic

Use

For temporary relief of pain and/or itching associated with minor burns, sunburn, minor cuts, scrapes and insect bites or minor skin irritations.

Warnings

- For external use only.

- Flammable, keep away from fire or flame

- Avoid contact with eyes; if this happens, rinse thoroughly with water

Do Not Use

With electrocautery procedures.

Stop Use

If irritation and redness develop.If condition worsens or if symptoms persist for more than 7 days, or clear up and occur again within a few days,discontinue use and consult a doctor.

Caution:Keep out of reach of children.

If swallowed, get medical help or contact a Poison Control Center right away.

Directions

- For adults and children 2 years of age and older, apply to affected area not more than 3-4 times daily.
- For children under 2 years of age, consult a doctor before use.

Other information

Store at room temperature 15^0 -30^0 C (59^0 - 86^0 F). Avoid excessive heat.

Inactive ingredients

Isopropyl Alcohol, Purified Water

Principal Display Panel

NDC 60913-031-01

Phoenix Healthcare Solutions, LLC

"An Innovative Medical Manufacturer"

Sting and Bite Pads

Medium

For Individual,Professional and Hospital Use

Saturated with 6% Benzocaine as a topical analgesic

Latex Free

100 Individual Pads